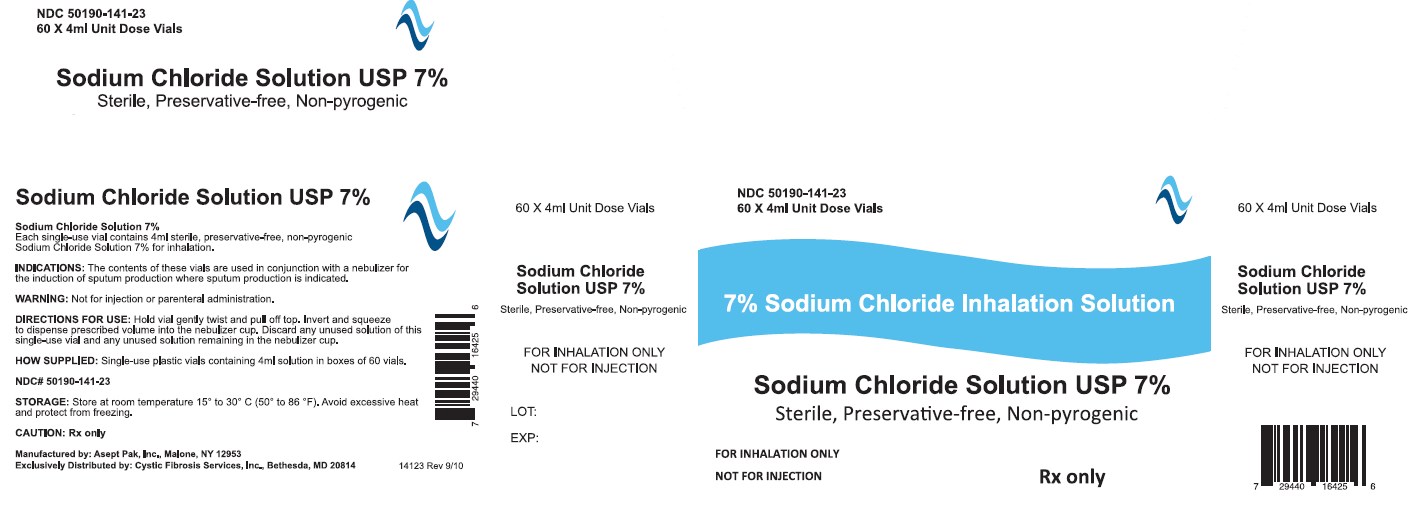 DRUG LABEL: Sodium Chloride Solution
NDC: 50190-141
Manufacturer: PharmaCaribe
Category: other | Type: MEDICAL DEVICE
Date: 20131120

ACTIVE INGREDIENTS: SODIUM CHLORIDE 280 mg/4 mL

Sodium Chloride Solution USP 7%

DESCRIPTION

Sodium Chloride Inhalation Solution USP 7% 4 mL

For Respiratory Therapy

Not for parenteral administration.

4 mL, 60 Vials Sterile Unit-Dose Vial

Discard any unused portion of the contents of this single-use vial as well as any unused solution remaining in the nebulizer cup.

Internal contents sterile. External surface of vial not sterile.

INDICATIONS AND USAGE

The contents of these vials are used in conjunction with a nebulizer for the induction of sputum production where sputum production is indicated.

INSTRUCTIONS FOR USE SECTION

Hold vial gently twist and pull off top. Invert and squeeze to dispense prescribed volume into the nebulizer cup.

How Supplied

Single-use plastic vials containing 4ml solution in cartons of 60 vials.

WARNINGS

Not for injection or parenteral administration.

STORAGE

Store at room temperature 15° to 30° C (50° to 86°F). Avoid excessive heat and protect from freezing.

Sodium Chloride Inhalation Solution USP 7% 4 mL

PRODUCT CODE 50190-141-23

Rx Only

Manufactured by: Asept Pak, Inc. , Malone, NY 12953

Exclusively Distributed by: Cystic Fibrosis Services, Inc. , Bethesda, MD 20814